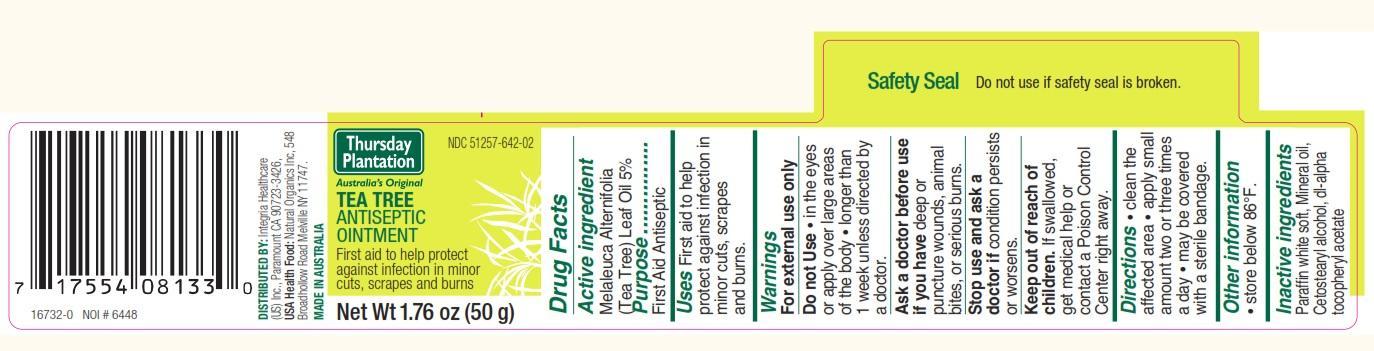 DRUG LABEL: Tea Tree Antiseptic
                
NDC: 51257-642 | Form: OINTMENT
Manufacturer: Integria Healthcare (US) Inc
Category: otc | Type: HUMAN OTC DRUG LABEL
Date: 20130827

ACTIVE INGREDIENTS: TEA TREE OIL 50 mg/1 g
INACTIVE INGREDIENTS: CETOSTEARYL ALCOHOL; MINERAL OIL; PARAFFIN; .ALPHA.-TOCOPHEROL ACETATE, DL-

Drug Facts

Active ingredient

Melaleuca Alternifolia (Tea Tree) Leaf Oil 5%

Purpose

First Aid Antiseptic

Uses

First aid to help protect against infection in minor cuts, scrapes and burns.

Warnings

For external use only

Do not Use

- in the eyes or apply over large areas of the body
- longer than 1 week unless directed by a doctor.

Ask a doctor before use if you have

deep or puncture wounds, animal bites, or serious burns.

Stop use and ask a doctor if

condition persists or worsens.

Keep out of reach of children.

OTHER SAFETY INFORMATION

If swallowed, get medical help or contact a Poison Control Center right away.

Directions

- clean the affected area
- apply small amount two or three times a day
- may be covered with a sterile bandage.

Other information

- store below 86 F.

Inactive ingredients

Paraffin white soft, Mineral oil, Cetostearyl alcohol, dl-alpha tocopheryl acetate

DESCRIPTION

DISTRIBUTED BY: Integria Healthcare (US) Inc., Paramount CA 90723-3426.

USA Health Food: Natural Organics Inc, 548 Broadhollow Road Melville NY 11747

MADE IN AUSTRALIA

Principal Display Panel

NDC 51257-642-02

Thursday Plantation

Australia's Original

TEA TREE ANTISEPTIC OINTMENT

First aid to help protect

against infection in minor

cuts, scrapes and burns

Net Wt 1.76 oz (50 g)